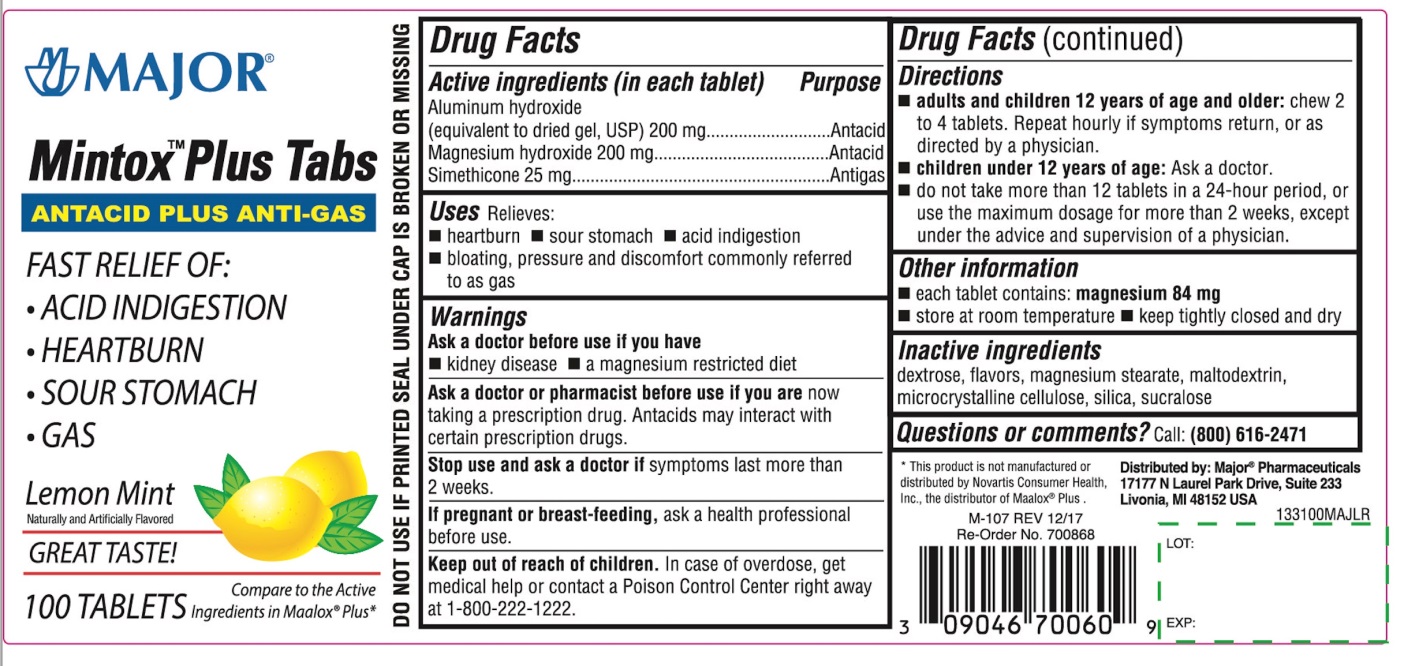 DRUG LABEL: Mintox Plus Tabs
NDC: 0904-6700 | Form: TABLET, CHEWABLE
Manufacturer: Major Pharmaceuticals
Category: otc | Type: HUMAN OTC DRUG LABEL
Date: 20250919

ACTIVE INGREDIENTS: ALUMINUM HYDROXIDE 200 mg/1 1; MAGNESIUM HYDROXIDE 200 mg/1 1; DIMETHICONE, UNSPECIFIED 25 mg/1 1
INACTIVE INGREDIENTS: DEXTROSE, UNSPECIFIED FORM; MAGNESIUM STEARATE; MALTODEXTRIN; MICROCRYSTALLINE CELLULOSE; SILICON DIOXIDE; SUCRALOSE

Major Mintox™ Plus Tabs Antacid Plus Anti-Gas Lemon Mint 100 Tablets

Active ingredients (in each tablet)

Aluminum hydroxide (equivalent to dried gel, USP) 200 mg
Magnesium hydroxide 200 mg
Simethicone 25mg

Purpose

Antacid
Antacid
Antigas

Uses

Relieves:

- heartburn
- sour stomach
- acid indigestion
- bloating, pressure and discomfort commonly referred to as gas

Warnings

Ask a doctor before use if you have

- kidney disease
- a magnesium-restricted diet

Ask a doctor or pharmacist before use if you are

now taking a prescription drug. Antacids may interact with certain prescription drugs.

Stop use and ask a doctor if

symptoms last more than 2 weeks.

If Pregnant or breast -feeding

ask a health professional before use.

Keep out of reach of children.

In case of overdose, get medical help or contact a Poison Control Center right away at 1-800-222-1222.

Directions

- adults and children 12 years of age and older:chew 2 to 4 tablets. Repeat hourly if symptoms return, or as directed by a physician .
- children under 12 years of age :Ask a doctor.
- do not take more than 12 tablets in a 24- hour period, or use the maximum dosage for more than 2 weeks ,except under the advice and supervision of a physician.

Other information

- each tablet contains: magnesium 84 mg
- store at room temperature
- keep tightly closed and dry

Inactive ingredients

dextrose, flavors, magnesium stearate, maltodextrin, microcrystalline cellulose, silica, sucralose

Questions or comments?

Call : (800)-616-2471

Principal Display Panel

MAJOR®

Mintox™ Plus Tabs

ANTACID PLUS ANTI-GAS

FAST RELIEF OF:

- ACID INDIGESTION
- HEARTBURN
- SOUR STOMACH
- GAS

Lemon Mint

Naturally and Artificially Flavored

GREAT TASTE!

100 TABLETS

Compare to the Active Ingredients in Maalox®Plus*

Distributed by:

Major®Pharmaceuticals

17177N Laurel park drive, Suite 233

Livonia, MI 48152 USA

*This product is not manufactured or distributed by Novartis Consumer Health Inc, the distributor of Maalox®plus.